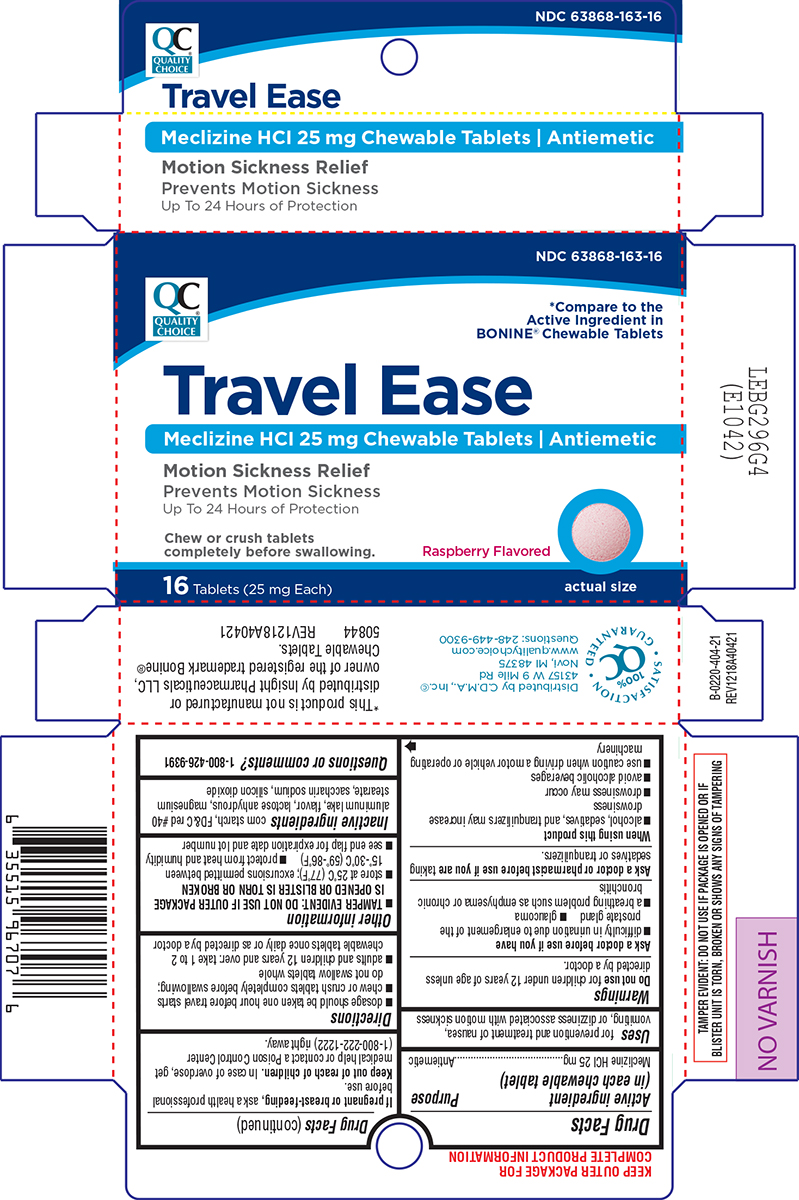 DRUG LABEL: Travel Ease
NDC: 63868-163 | Form: TABLET, CHEWABLE
Manufacturer: CHAIN DRUG MARKETING ASSOCIATION INC
Category: otc | Type: HUMAN OTC DRUG LABEL
Date: 20240828

ACTIVE INGREDIENTS: MECLIZINE HYDROCHLORIDE 25 mg/1 1
INACTIVE INGREDIENTS: STARCH, CORN; FD&C RED NO. 40; ANHYDROUS LACTOSE; MAGNESIUM STEARATE; SACCHARIN SODIUM; SILICON DIOXIDE

Quality Choice 44-404 DELISTED

Active ingredient (in each chewable tablet)

Meclizine HCl 25 mg

Purpose

Antiemetic

Uses

for prevention and treatment of nausea, vomiting, or dizziness associated with motion sickness

Warnings

Do not use

for children under 12 years of age unless directed by a doctor.

Ask a doctor before use if you have

- difficulty in urination due to enlargement of the prostate gland
- glaucoma
- a breathing problem such as emphysema or chronic bronchitis

Ask a doctor or pharmacist before use if you are

taking sedatives or tranquilizers.

When using this product

- alcohol, sedatives, and tranquilizers may increase drowsiness
- drowsiness may occur
- avoid alcoholic beverages
- use caution when driving a motor vehicle or operating machinery

If pregnant or breast-feeding,

ask a health professional before use.

Keep out of reach of children.

In case of overdose, get medical help or contact a Poison Control Center right away.

Directions

- dosage should be taken one hour before travel starts
- chew or crush tablets completely before swallowing; do not swallow tablets whole
- adults and children 12 years and over: take 1 to 2 chewable tablets once daily or as directed by a doctor

Other information

- TAMPER EVIDENT: DO NOT USE IF OUTER PACKAGE IS OPENED OR BLISTER IS TORN OR BROKEN
- store at 25°C (77°F); excursions permitted between 15°-30°C (59°-86°F)
- protect from heat and humidity
- see end flap for expiration date and lot number

Inactive ingredients

corn starch, FD&C red #40 aluminum lake, flavor, lactose anhydrous, magnesium stearate, saccharin sodium, silicon dioxide

Questions or comments?

1-800-426-9391

Principal Display Panel

NDC 63868-163-16

QC
QUALITY
CHOICE®

*Compare to the
Active Ingredient in
BONINE® Chewable Tablets

Travel Ease
Meclizine HCI 25 mg Chewable Tablets | Antiemetic
Motion Sickness Relief
Prevents Motion Sickness
Up To 24 Hours of Protection

Chew or crush tablets
completely before swallowing.

Raspberry Flavored

16 Tablets (25 mg Each)

actual size

TAMPER EVIDENT: DO NOT USE IF PACKAGE IS OPENED OR IF
BLISTER UNIT IS TORN, BROKEN OR SHOWS ANY SIGNS OF TAMPERING

*This product is not manufactured or
distributed by Insight Pharmaceuticals LLC,
owner of the registered trademark Bonine®
Chewable Tablets.
50844 REV1218A40421

Distributed by C.D.M.A., Inc.©
43157 W 9 Mile Rd
Novi, MI 48375
www.qualitychoice.com
Questions: 248-449-9300

100%
QC
Satisfaction
Guaranteed

Quality Choice 44-404